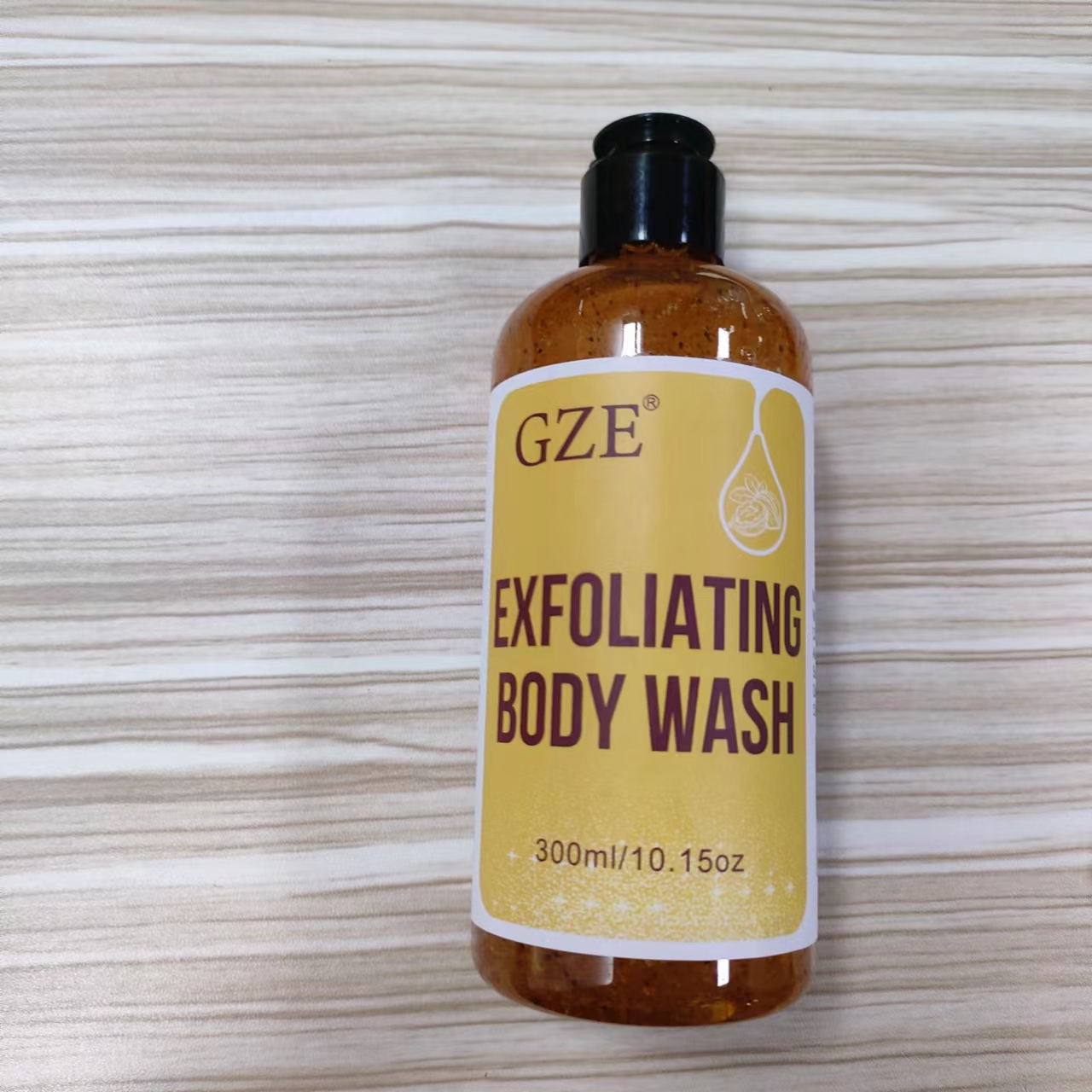 DRUG LABEL: GZE EXFOLIATING BODY WASH
NDC: 74458-243 | Form: LOTION
Manufacturer: Guangzhou Yilong Cosmetics Co., Ltd
Category: otc | Type: HUMAN OTC DRUG LABEL
Date: 20241118

ACTIVE INGREDIENTS: JUGLANS REGIA SHELL 8 g/100 mL; COCONUT SHELL 5 g/100 mL
INACTIVE INGREDIENTS: AQUA; POWDERED CELLULOSE; CITRIC ACID MONOHYDRATE; GLYCERIN; SODIUM HYDROXIDE

GZE EXFOLIATING BODY WASH

ACTIVE INGREDIENT

Juglans Regia (Walnut) Shell Powder 8%
Cocos Nucifera (Coconut) Shell Powder 5%

INACTIVE INGREDIENT

Aqua

Glycerin

Cellulose

Citric Acid

Sodium Hydroxide

Fragrance

INDICATIONS AND USAGE

Apply all over the body, scrub and rinse off.

PURPOSE

Exfoliating.

WARNINGS

For external use only.

Stop use and ask a doctor if rash occurs.

Do not use on damaged or broken skin.

When using this product keep out of eyes. Rinse with water to remove.

Keep out of reach of children. If swallowed, get medical help or contact a Poison Control Center right away.

DOSAGE AND ADMINISTRATION

Apply all over the body,
scrub and rinse off.